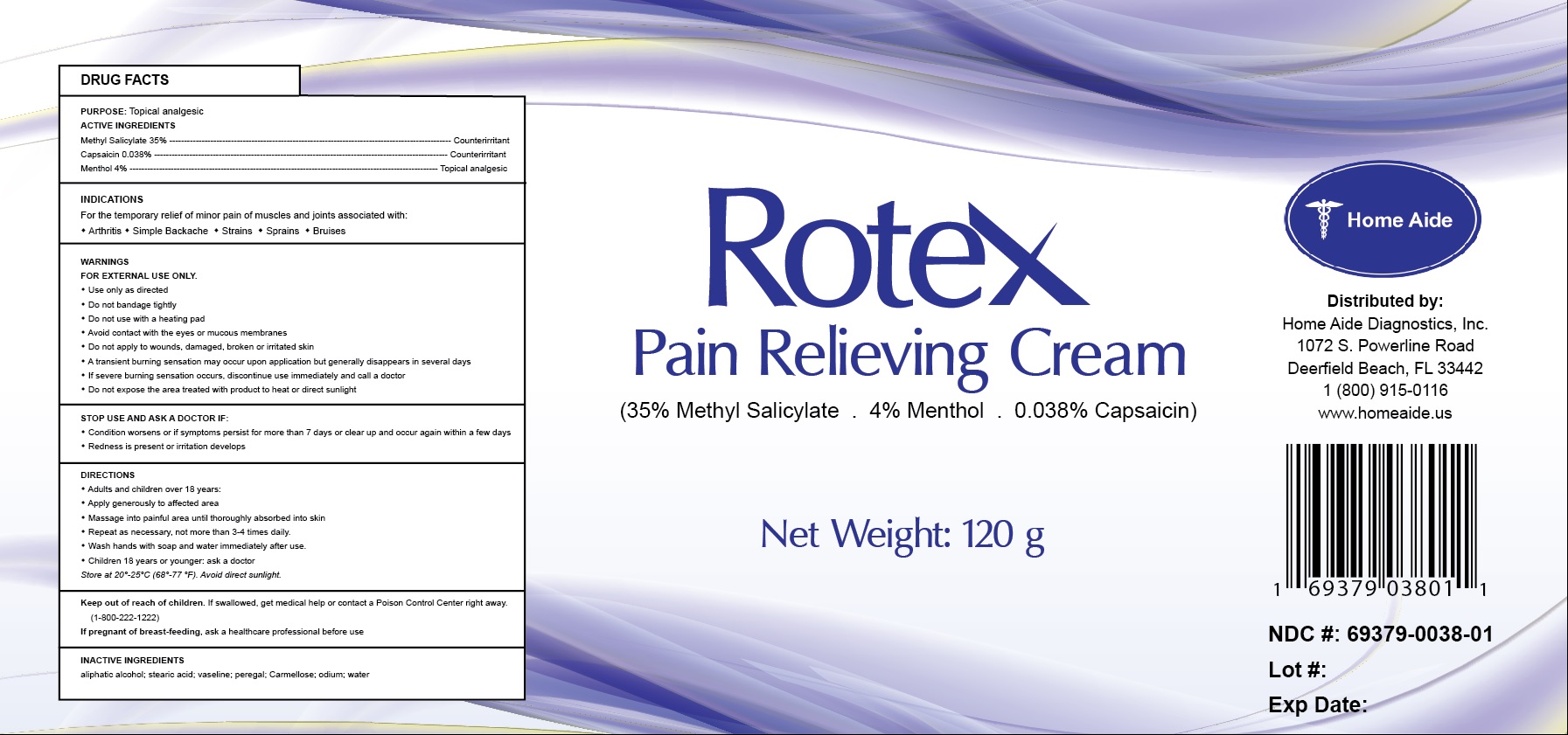 DRUG LABEL: Rotex
NDC: 69379-038 | Form: CREAM
Manufacturer: Home Aide Diagnostics, Inc.
Category: otc | Type: HUMAN OTC DRUG LABEL
Date: 20150804

ACTIVE INGREDIENTS: METHYL SALICYLATE 35 g/100 g; MENTHOL 4 g/100 g; CAPSAICIN 0.038 g/100 g
INACTIVE INGREDIENTS: STEARIC ACID

Rotex Pain Relieving Cream

PURPOSE: Topical analgesic

ACTIVE INGREDIENTS
Methyl Salicylate 35% ----------------------------- Counterirritant
Capsaicin 0.038% ----------------------------------- Counterirritant
Menthol 4% ---------------------------------------- Topical analgesic

INDICATIONS
For the temporary relief of minor pain of muscles and joints associated with:

- Arthritis
- Simple Backache
- Strains
- Sprains
- Bruises

WARNINGS
FOR EXTERNAL USE ONLY.

- Use only as directed
- Do not bandage tightly
- Do not use with a heating pad
- Avoid contact with the eyes or mucous membranes
- Do not apply to wounds, damaged, broken or irritated skin
- A transient burning sensation may occur upon application but generally disappears in several days
- If severe burning sensation occurs, discontinue use immediately and call a doctor
- Do not expose the area treated with product to heat or direct sunlight

DIRECTIONS

- Adults and children over 18 years:
- Apply generously to affected area
- Massage into painful area until thoroughly absorbed into skin
- Repeat as necessary, not more than 3-4 times daily.
- Wash hands with soap and water immediately after use.
- Children 18 years or younger: ask a doctor

Store at 20°-25°C (68°-77 °F). Avoid direct sunlight.

STOP USE AND ASK A DOCTOR IF:

- Condition worsens or if symptoms persist for more than 7 days or clear up and occur again within a few days
- Redness is present or irritation develops

Keep out of reach of children. If swallowed, get medical help or contact a Poison Control Center right away. (1-800-222-1222)

PREGNANCY OR BREAST FEEDING

If pregnant of breast-feeding, ask a healthcare professional before use

INACTIVE INGREDIENTS
aliphatic alcohol; stearic acid; vaseline; peregal; Carmellose; odium; water